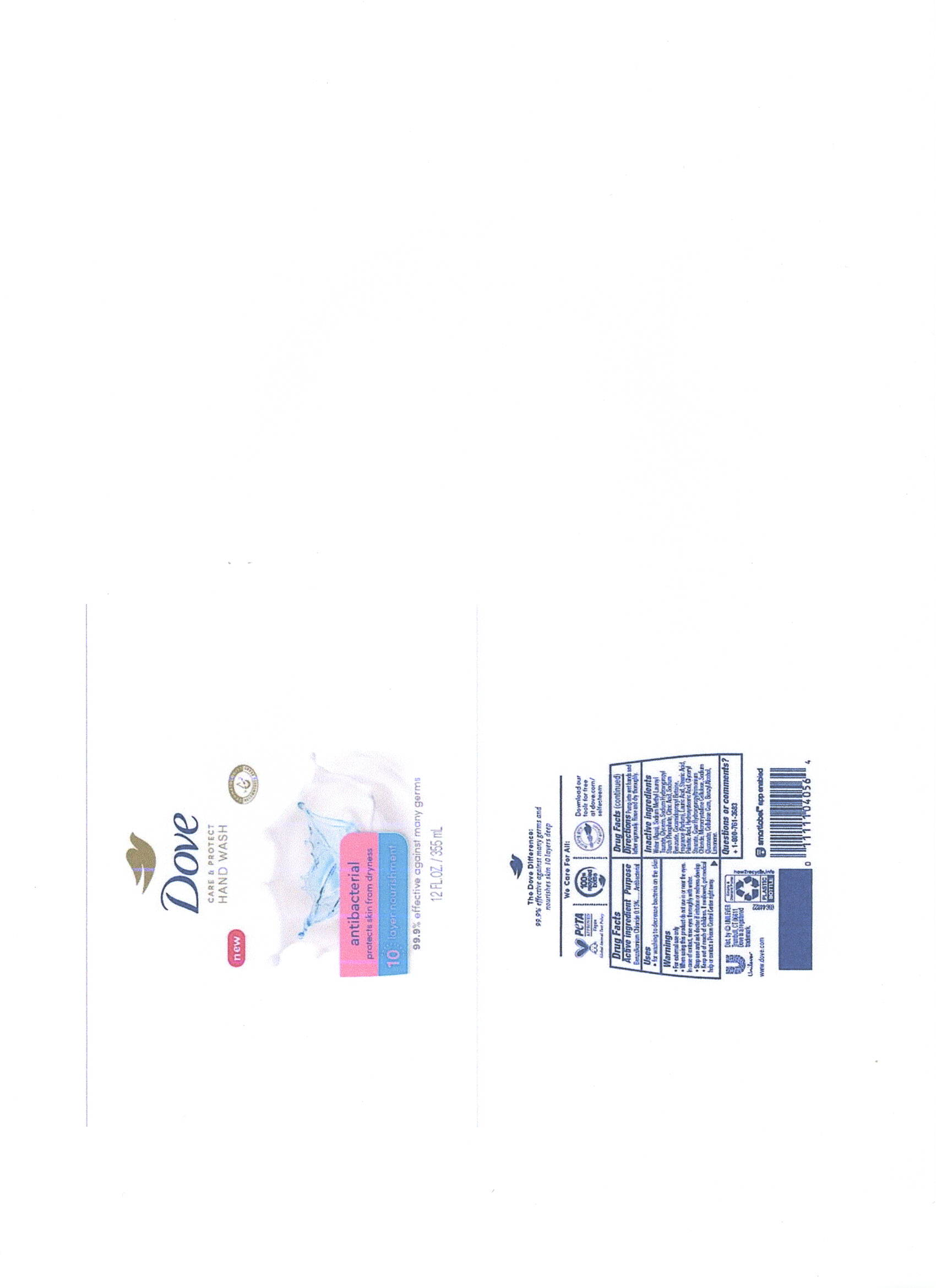 DRUG LABEL: Dove
NDC: 64942-2105 | Form: LIQUID
Manufacturer: Conopco Inc. d/b/a/ Unilever
Category: otc | Type: HUMAN OTC DRUG LABEL
Date: 20241107

ACTIVE INGREDIENTS: BENZALKONIUM CHLORIDE 1.3 mg/1 mL
INACTIVE INGREDIENTS: SODIUM LAUROYL METHYL TAURATE; STEARIC ACID; CITRIC ACID MONOHYDRATE; WATER; GLYCERIN; COCAMIDOPROPYL BETAINE; PALMITIC ACID; LAURIC ACID; SODIUM BENZOATE; 12-HYDROXYSTEARIC ACID; GLYCERYL MONOSTEARATE; CELLULOSE, MICROCRYSTALLINE; SODIUM GLUCONATE; CARBOXYMETHYLCELLULOSE SODIUM, UNSPECIFIED FORM; BENZYL ALCOHOL; LIMONENE, (+)-

Dove Care & Protect Antibacterial Hand Wash

DOVE CARE & PROTECT ANTIBACTERIAL HAND WASH - Benzalkonium Chloride

Dove Care & Protect Antibacterial Hand Wash

Drug Facts

Active ingredient

Benzalkonium Chloride 0.13%

Purpose

Antibacterial

Uses

For washing to decrease bacteria on the skin

Warnings

• For external use only
• When using this product do not use in or near the eyes. In case of contact, rinse eyes thoroyghly with water.
• Stop use and ask doctor if irritation or redness develop

If swallowed, get medical help or contact a Poison Control Center right away.

• Keep out of reach of children except under adult supervision.

If swallowed, get medical help or contact a poison control Center right away.

Directions

Pump into wet hands and lather vigorously. Rinse and dry thoroughtly

Inactive ingredients

Water, Sodium Methyl Lauroyl Taurate, Glycerin, Sodium Hydroxypropyl Starch Phosphate, Citric Acid, Sodium Benzoate, Cocamidopropyl Betaine, Fragrance (Parfum), Lauric Acid, Stearic Acid, Palmitic Acid, Hydroxystearic Acid, Glyceryl Stearate, Guar Hydroxypropyltrimonium Chloride, Microcrystalline Cellulose, Sodium Gluconate, Cellulose Gum, Benzyl Alcohol, Limonene.

Questions or Comments?

1-800-761-3683